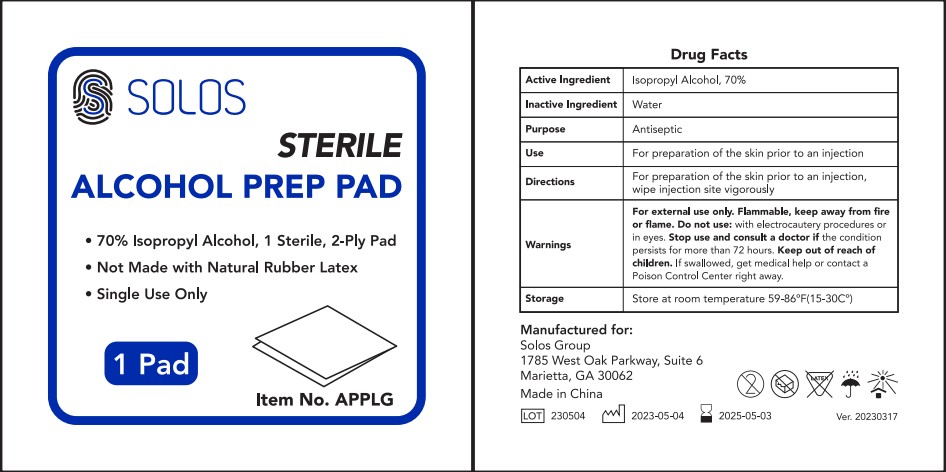 DRUG LABEL: Solos Sterile Alcohol Prep Pad
NDC: 69139-606 | Form: SWAB
Manufacturer: YIWU HAODING MEDICAL CO.,LTD
Category: otc | Type: HUMAN OTC DRUG LABEL
Date: 20230325

ACTIVE INGREDIENTS: ALCOHOL 70 g/100 g
INACTIVE INGREDIENTS: WATER

DRUG FACTS

Active Ingredient

Isopropyl Alcohol 70%

Purpose

Antiseptic

Uses:

For preparation of the skin prior to an injection, wipe injection site vigorously.

Discard after single use.

Other Information: Store atRoom temperature 59-86℉（15-30℃).

WARNINGS

For external use only.

Flammable, keep away from heat and flame.

Do not use: with electrocautery procedures or in eyes.

Stop use and consult a doctor if the condition persists for more than 72 hours.

Keep out of reach of children.

If swallowed, get medical help or contact a Poison Control Center right away.

Inactive Ingredients:

water